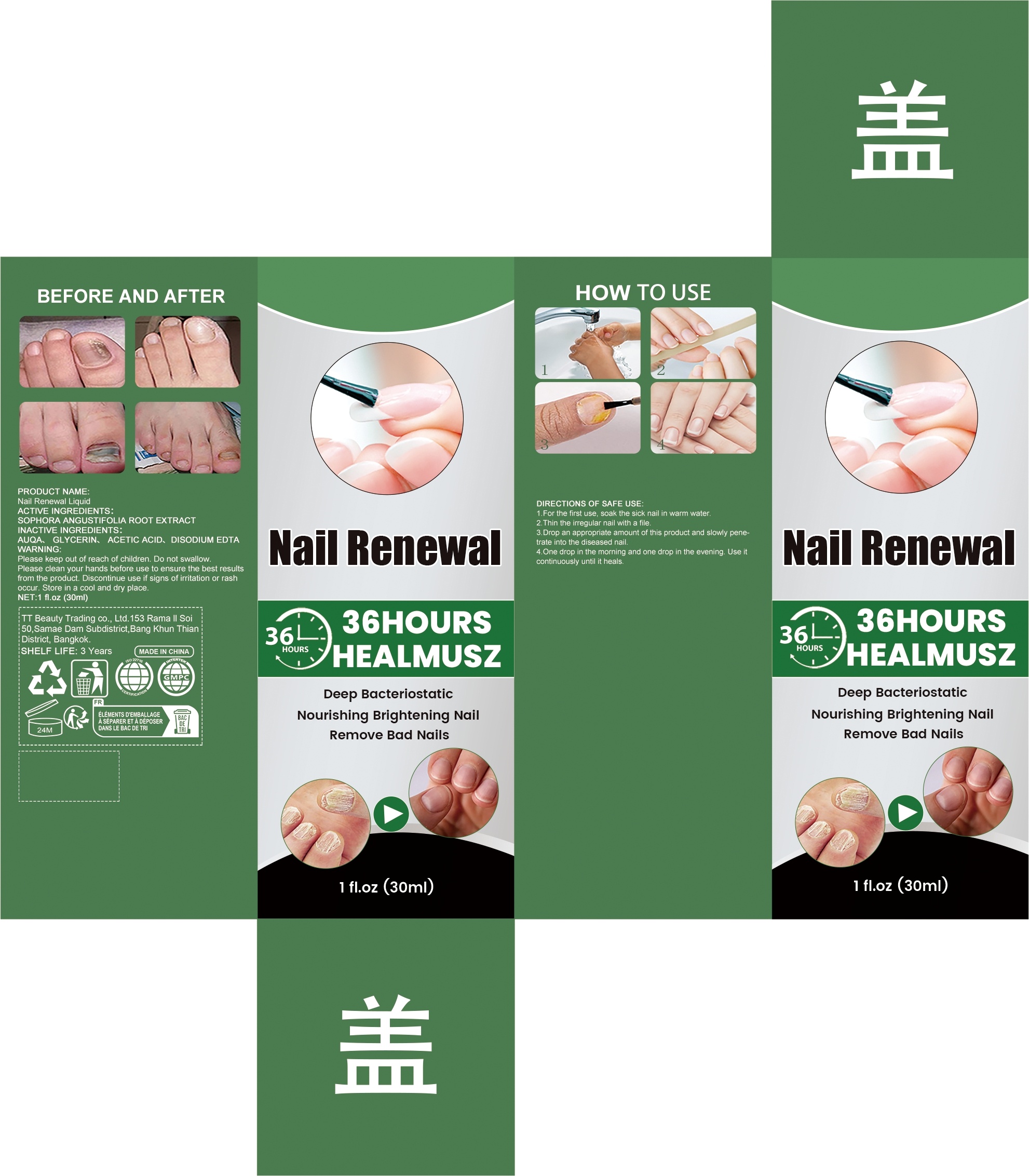 DRUG LABEL: Nail Renewal Liquid
NDC: 85206-004 | Form: LIQUID
Manufacturer: TT Beauty Trading Co., Ltd.
Category: otc | Type: HUMAN OTC DRUG LABEL
Date: 20250827

ACTIVE INGREDIENTS: SOPHORA FLAVESCENS ROOT 0.42 mg/30 mg
INACTIVE INGREDIENTS: AQUA 28.2 mg/30 mg; GLYCERIN 1.2 mg/30 mg; ACETIC ACID 0.15 mg/30 mg; EDETATE DISODIUM 0.03 mg/30 mg

ACTIVE INGREDIENT

SOPHORA ANGUSTIFOLIA ROOT

WHEN USING

1.For the first use, soak the sick nail in warm water.
2.Thin the irregular nail with a file.
3.Drop an appropriate amount of this product and slowly penetrate into the diseased nail.
4.One drop in the morning and one drop in the evening. Use it continuously until it heals.

PURPOSE

Deep Bacteriostatic
Nourishing Brightening Nail
Remove Bad Nails

WARNINGS

Please keep out of reach of children. Do not swallow. Please clean your hands before use to ensure the best results from the product. Discontinue use if signs of irritation or rash occur. Store in a cool and dry place.

DO NOT USE

Discontinue use if signs of irritation or rash occur.

STOP USE

Discontinue use if signs of irritation or rash occur.

KEEP OUT OF REACH OF CHILDREN

Please keep out of reach of children. Do not swallow.

STORAGE AND HANDLING

Store in a cool and dry place.

INACTIVE INGREDIENT

AQUA、 GLYCERIN、 ACETIC ACID、DISODIUM EDTA

DOSAGE AND ADMINISTRATION

One drop in the morning and one drop in the evening. Use it continuously until it heals.

INDICATIONS AND USAGE

One drop in the morning and one drop in the evening. Use it continuously until it heals.